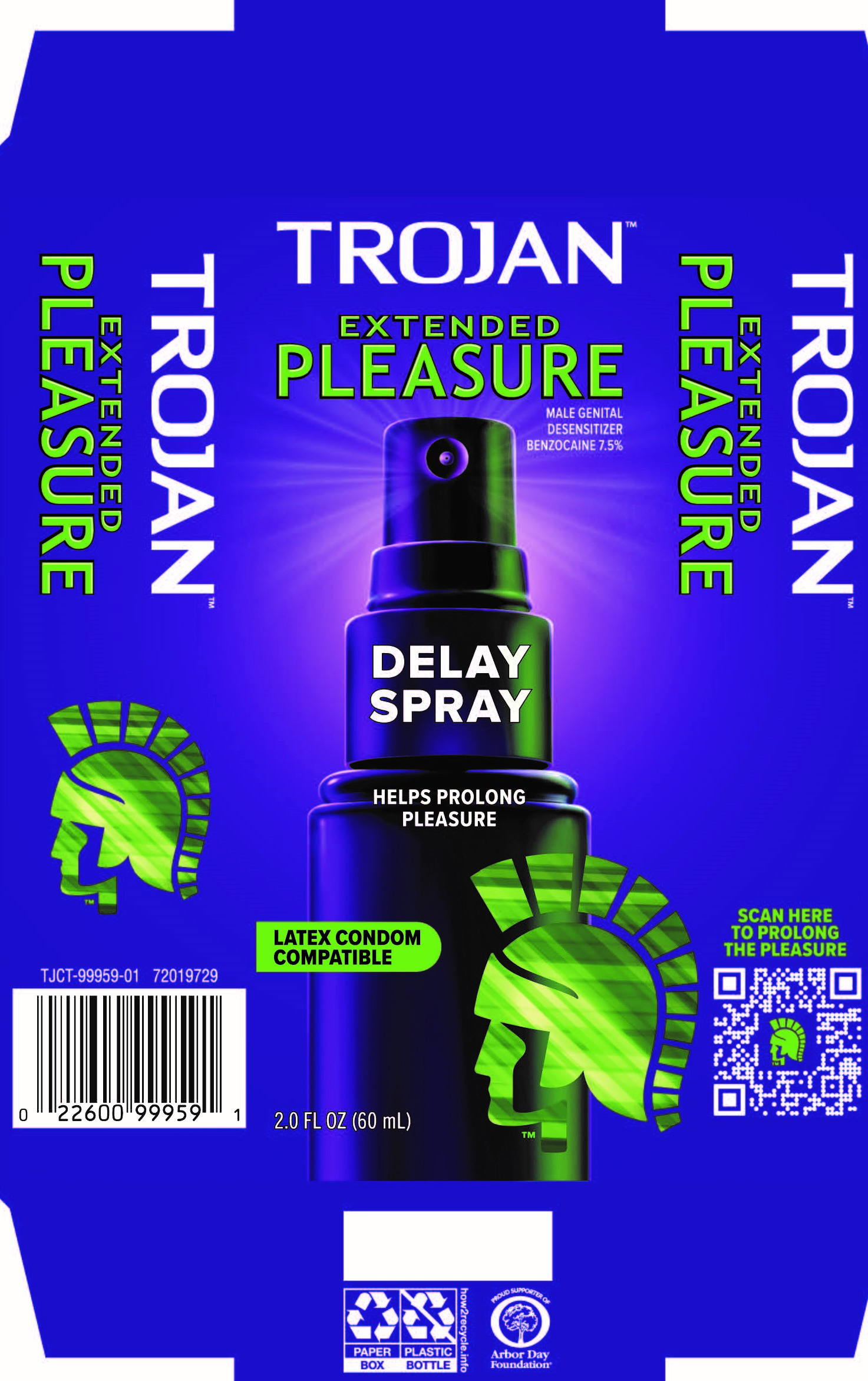 DRUG LABEL: Trojan Extended Pleasure
NDC: 10237-200 | Form: SPRAY
Manufacturer: Church & Dwight Co., Inc.
Category: otc | Type: HUMAN OTC DRUG LABEL
Date: 20251209

ACTIVE INGREDIENTS: BENZOCAINE 4.5 g/60 mL
INACTIVE INGREDIENTS: POLYETHYLENE GLYCOL 400; WATER; PROPYLENE GLYCOL

Trojan Extended Pleasure Delay Spray

ACTIVE INGREDIENT

Benzocaine 7.5%

PURPOSE

Male Genital Desensitizer

INDICATIONS AND USAGE

- Helps in the prevention of premature ejaculation.
- Helps in temporarily prolonging the time until ejaculation.

WARNINGS

For external use only.

Premature ejaculation may be due to a condition requiring medical supervision. If this product, used as directed, does not provide relief, discontinue use and consult a doctor.

Avoid contact with the eyes.

If you or your partner develop a rash or irritation, such as burning or itching, discontinue use. If symptoms persist, consult a doctor.

PREGNANCY OR BREAST FEEDING

If pregnant or breastfeeding,ask a health professional before use.

Keep out of reach of children.

If swallowed, get medical help or contact a Poison Control Center right away.

Directions

- Apply a small amount to the head and shaft of the penis before intercourse, or use as directed by a doctor. Wash product off after intercourse.
- Use only on intact, non-inflamed skin.
- Allow product to dry prior to intercourse.
- Use as directed, not more than four times per day.
- Not suitable for oral use.

Other information

- Store between 20-30°C (68-86ºF).
- Compatible with latex condoms.
- Do not use if carton safety seal is broken or missing.

INACTIVE INGREDIENT

PEG-8, Propylene Glycol, Water (Aqua)

Questions?

Call or text 1-800-320-3075 M-F 9AM-5PM ET

PACKAGE LABEL

TROJAN™

EXTENDED

PLEASURE

MALE GENITAL

DESENSITIZER

BENZOCAINE 7.5%

DELAY

SPRAY

HELPS PROLONG

PLEASURE

LATEX CONDOM

COMPATIBLE

2.0 FL OZ (60 mL)